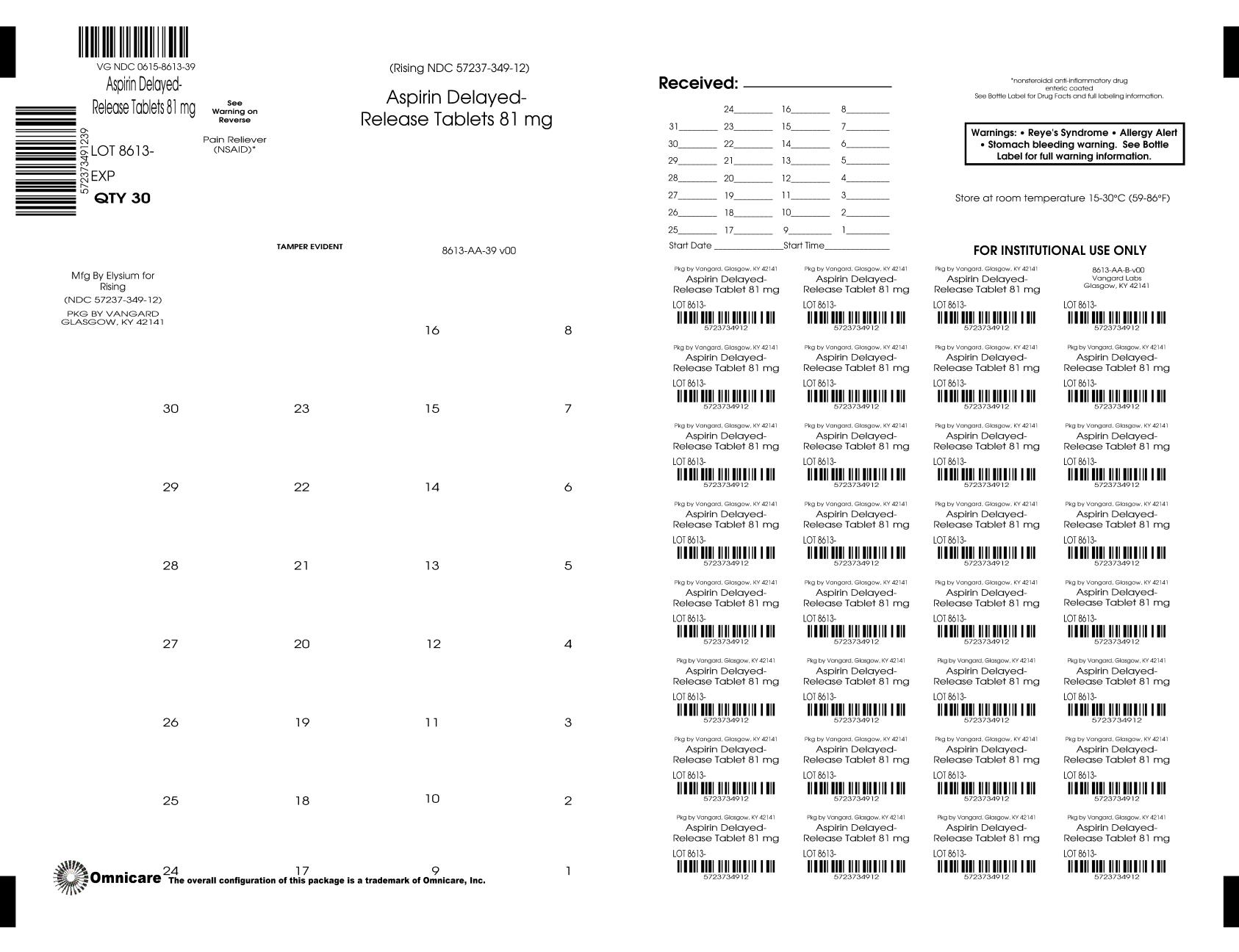 DRUG LABEL: Adult Low Dose Aspirin
NDC: 0615-8613 | Form: TABLET, DELAYED RELEASE
Manufacturer: NCS HealthCare of KY, LLC dba Vangard Labs
Category: otc | Type: HUMAN OTC DRUG LABEL
Date: 20260123

ACTIVE INGREDIENTS: ASPIRIN 81 mg/1 1
INACTIVE INGREDIENTS: SILICON DIOXIDE; CROSCARMELLOSE SODIUM; D&C YELLOW NO. 10; FERRIC OXIDE YELLOW; LACTOSE, UNSPECIFIED FORM; METHACRYLIC ACID AND ETHYL ACRYLATE COPOLYMER; MICROCRYSTALLINE CELLULOSE; POLYSORBATE 80; sodium hydroxide; TALC; TITANIUM DIOXIDE; TRIETHYL CITRATE

Compare to the active ingredient in Bayer® Low Dose Aspirin†
Adult Low Dose
Aspirin
81 mg
Pain Reliever (NSAID)
adult aspirin regimen use
delayed release
safe pain relief
SEE NEW WARNINGS INFORMATION

DO NOT USE IF IMPRINTED SAFETY SEAL UNDER CAP IS BROKEN OR MISSING.

Drug Facts

Active ingredient (in each tablet) Purpose
Aspirin 81 mg (NSAID)*..................................Pain reliever
*nonsteroidal anti-inflammatory drug

Uses

- temporary relief of minor aches and pains or as recommended by your doctor.
  Because of its delayed release action, this product will not provide fast relief of headache or symptoms needing immediate relief.

Warnings

Reye’s syndrome: Children and teenagers who have or are recovering from chicken pox or flu-like symptoms should not use this product. When using this product, if changes in behavior with nausea and vomiting occur, consult a doctor because these symptoms could be an early sign of Reye’s syndrome, a rare but serious illness.

Allergy alert: Aspirin may cause a severe allergic reaction, which may include:

- hives
- shock
- facial swelling
- asthma (wheezing)

Stomach bleeding warning: This product contains an NSAID, which may cause severe stomach bleeding.

The chance is higher if you:

- are age 60 or older
- have had stomach ulcers or bleeding problems
- take a blood thinning (anticoagulant) or steroid drug
- take other drugs containing prescription or nonprescription NSAIDs [aspirin, ibuprofen, naproxen, or others]
- have 3 or more alcoholic drinks every day while using this product
- take more or for a longer time than directed

Do not use

- if you are allergic to aspirin, or any other pain reliever/fever reducer

Ask a doctor before use if

- You have asthma
- stomach bleeding warning applies to you
- you have a history of stomach problems, such as heartburn
- you have high blood pressure, heart disease, liver cirrhosis or kidney disease
- you are taking a diuretic

Ask a doctor or pharmacist before use if you are

- taking a prescription drug for diabetes, gout, or arthritis
- under a doctor’s care for any serious condition
- taking any other drug

Stop use and ask a doctor if

- you experience any of the following signs of stomach
  bleeding:
- feel faint
- has bloody or black stools
- vomits blood
- has stomach pain that does not get better
- an allergic reaction occurs. Seek medical help right away.
- ringing in the ears or loss of hearing occurs
- pain gets worse or lasts for more than 10 days
- fever get worse or lasts for more than 3 days
- redness or swelling is present in the painful area
- new symptoms appear. These could be sign of a serious condition.

PREGNANCY OR BREAST FEEDING

If pregnant or breast-feeding, ask a health professional before use. It is especially important not to use aspirin during the last 3 months of pregnancy unless definitely directed to do so by a doctor because it may cause problems in the unborn child or complications during delivery.

Keep out of reach of children.

In case of overdose, get medical help or contact a Poison Control Center (1-800-222-1222) right away. Quick medical attention is critical for adults as well as for children even if you do not notice any signs or symptoms.

Directions

- drink a full glass of water with each dose
- adults and children 12 years and over:
- take 4 to 8 tablets every 4 hours while symptoms last
- do not take more than 48 tablets in 24 hours unless directed by doctor
- children under 12 years: ask a doctor

Other information

- store at room temperature 15-30°C (59-86°F)

Inactive ingredients

Colloidal silicon dioxide, croscarmellose sodium, D&C yellow 10, iron oxide yellow 6, lactose, methacrylic acid and ethyl acrylate copolymer,
microcrystalline cellulose, polysorbate 80, sodium hydroxide, talc, titanium dioxide, triethyl citrate

Questions and comments? Call 1-844-474-7464

†This product is not manufactured or distributed by Bayer, owner of the registered trademark Aspirin Regimen BAYER®

Distributed by:
Rising Pharma Holdings, Inc.
East Brunswick, NJ 08816

Made in India

Mfg. Lic. No.: G/25/1362
Issued: 06/2025
S-063